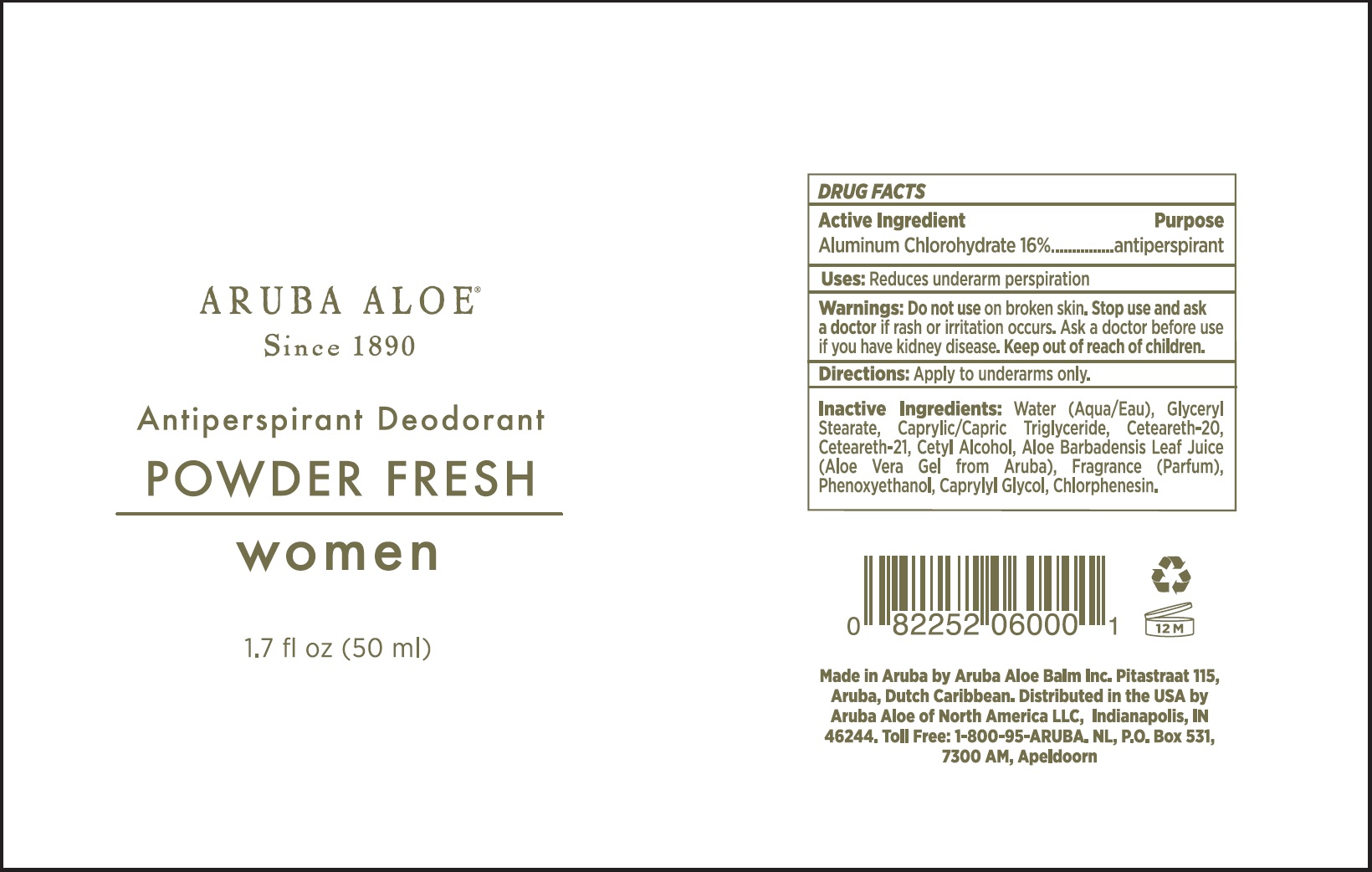 DRUG LABEL: Antiperspirant Deodorant Fresh Women
NDC: 53675-163 | Form: LOTION
Manufacturer: Aruba Aloe Balm NV
Category: otc | Type: HUMAN OTC DRUG LABEL
Date: 20231106

ACTIVE INGREDIENTS: ALUMINUM CHLOROHYDRATE 160 mg/1 mL
INACTIVE INGREDIENTS: WATER; GLYCERYL MONOSTEARATE; MEDIUM-CHAIN TRIGLYCERIDES; POLYOXYL 20 CETOSTEARYL ETHER; CETYL ALCOHOL; ALOE VERA LEAF; PHENOXYETHANOL; CAPRYLYL GLYCOL; CHLORPHENESIN

Antiperspirant Deodorant Powder Fresh Women

Active Ingredient

Aluminum Chlorohydrate 16%

Purpose

antiperspirant

Uses:

Reduces underarm perspiration

Warnings:

Do not use

on broken skin.

Stop use and ask a doctor

if rash or irritation occurs. Ask a doctor before use if you have kidney disease

Directions:

Apply to underarms only.

Inactive Ingredients:

Water (Aqua/Eau), Glyceryl Stearate, Caprylic/Capric Triglyceride, Ceterateh-20, Ceteareth-21, Cetyl Alcohol, Aloe Barbadensis Leaf Juice (Aloe Vera Gel from Aruba), Fragrance (Parfum), Phenoxyethanol, Caprylyl Glycol, Chlorphenesin.